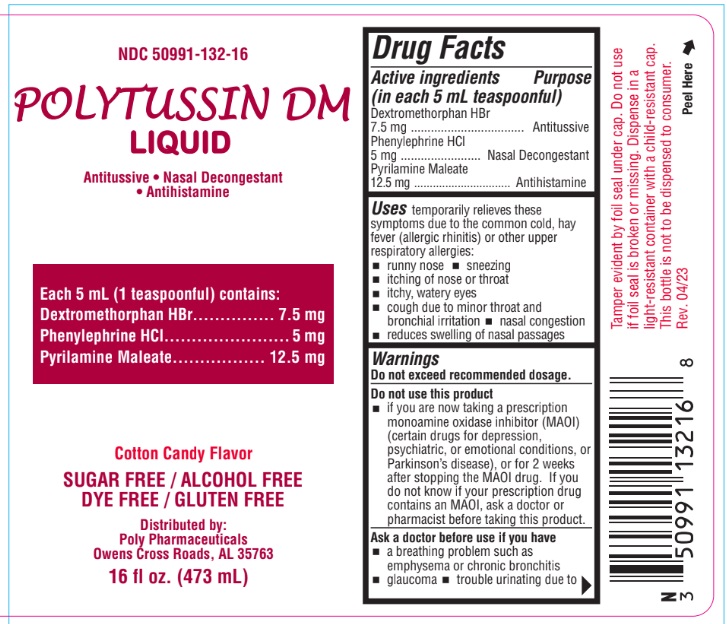 DRUG LABEL: Polytussin DM
NDC: 50991-132 | Form: SYRUP
Manufacturer: Poly Pharmaceuticals, Inc.
Category: otc | Type: HUMAN OTC DRUG LABEL
Date: 20251219

ACTIVE INGREDIENTS: DEXTROMETHORPHAN HYDROBROMIDE 7.5 mg/5 mL; PYRILAMINE MALEATE 12.5 mg/5 mL; PHENYLEPHRINE HYDROCHLORIDE 5 mg/5 mL
INACTIVE INGREDIENTS: ANHYDROUS CITRIC ACID; SORBITOL; WATER; METHYLPARABEN; PROPYLENE GLYCOL; SUCRALOSE; POTASSIUM CITRATE; PROPYLPARABEN

Polytussin DM

Active ingredients

(in each 5 mL teaspoonful)

Dextromethorphan HBr............... 7.5 mg
Phenylephrine HCl....................... 5 mg
Pyrilamine Maleate................. 12.5 mg

Ask a doctor or pharmacist before use if you are taking sedatives or tranquilizers.

Uses

temporarily relieves these symptoms due to the common cold, hay fever (allergic rhinitis) or other upper respiratory allergies:

- runny nose
- sneezing
- itching of nose or throat
- itchy, watery eyes
- cough due to minor throat and bronchial irritation
- nasal congestion
- reduces swelling of nasal passages

Warnings

Do not exceed recommended dosage.

Ask a doctor before use if you have

- a breathing problem such as emphysema or chronic bronchitis
- glaucoma
- trouble urinating due to an enlarged prostate gland
- a cough that lasts or is chronic such as occurs with smoking, asthma or emphysema
- a cough that occurs with too much phlegm (mucus)
- heart disease
- high blood

When using this product

- excitability may occur, especially in children
- may cause marked drowsiness
- avoid alcoholic drinks
- alcohol, sedatives, and tranquilizers may increase the drowsiness effect
- be careful when driving a motor vehicle or operating machinery

Stop use and ask a doctor if

- nervousness, dizziness, or sleeplessness occur
- cough or nasal congestion persists for more than 1 week, tends to recur, or is accompanied by a fever, rash or persistent headache. A persistent cough may be a sign of a serious condition.
- new symptoms occur

PREGNANCY OR BREAST FEEDING

If pregnant or breastfeeding ask a health professional before use

Keep out of reach of children. In case of overdose, get medical help or contact a Poison Control Center right away

Directions

Adults 12 and over: 10 mL every 4 hours

Not to exceed 60 mL in 24hours

Children 6-12: 5 mL every 4 hours,

Not to exceed 30 mL in 24hrs

Children 2-6: Consult a doctor

Other information

Store at room temperature 15°C-30°C (59°F-86°F)

Questions? Comments? Serious side effects associated with use of this product may be reported to this number. Call 1-800-882-1041
Mon. - Fri. (8 a.m. to 5 p.m. CST).

Inactive ingredients

Citric Acid, Flavor, Methylparaben, Potassium Citrate, Propylene Glycol, Propylparaben, Purified water, Sucralose,Sorbitol

PURPOSE

Antihistamine

Cough Suppressant

Nasal Decongestant